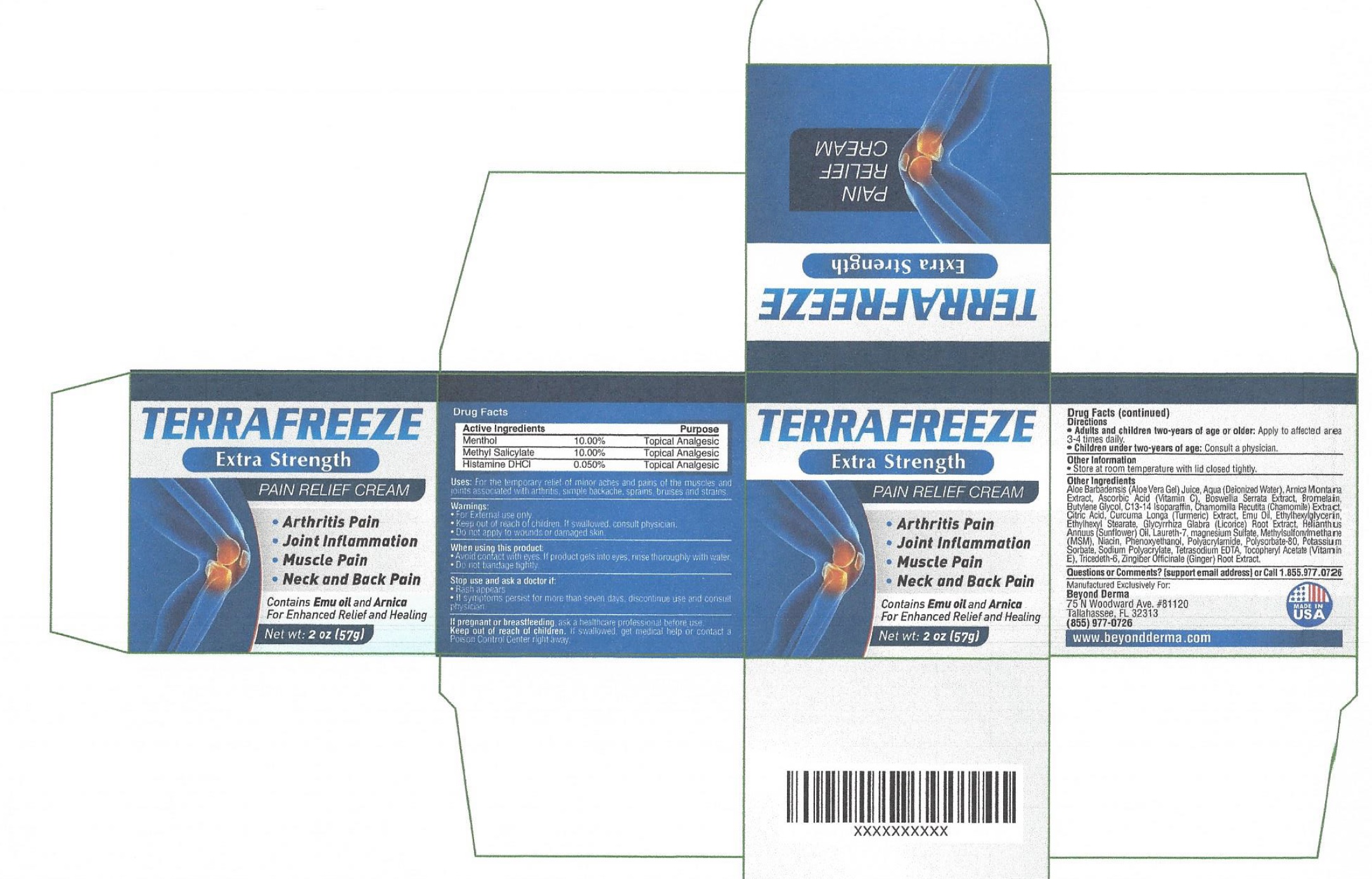 DRUG LABEL: TerraFreeze Pain Relief
NDC: 71805-855 | Form: CREAM
Manufacturer: Beyond Derma, LLC
Category: otc | Type: HUMAN OTC DRUG LABEL
Date: 20231111

ACTIVE INGREDIENTS: MENTHOL 100 mg/1 g; METHYL SALICYLATE 100 mg/1 g; HISTAMINE DIHYDROCHLORIDE 0.5 mg/1 g
INACTIVE INGREDIENTS: ALOE VERA LEAF; WATER; ARNICA MONTANA; ASCORBIC ACID; INDIAN FRANKINCENSE; BROMELAINS; BUTYLENE GLYCOL; C13-14 ISOPARAFFIN; MATRICARIA CHAMOMILLA; CITRIC ACID MONOHYDRATE; TURMERIC; EMU OIL; ETHYLHEXYLGLYCERIN; ETHYLHEXYL STEARATE; LICORICE; SUNFLOWER OIL; LAURETH-7; MAGNESIUM SULFATE, UNSPECIFIED; DIMETHYL SULFONE; NIACIN; PHENOXYETHANOL; POLYSORBATE 80; POTASSIUM SORBATE; EDETATE SODIUM; .ALPHA.-TOCOPHEROL ACETATE; TRIDECETH-6; GINGER

TerraFreeze Pain Relief Cream

Active Ingredients

Menthol 10.00%

Methyl Salicylate 10.00%

Histamine DHCl 0.050%

Purpose

Topical Analgesic

Uses:

For the temporary relief of minor aches and pains of the muscles and joints associated with arhritis, simple backache, sprains, bruises and strains.

Warnings:

- For External use only
- Keep out of reach of children. If swallowed, consult physician.
- Do not apply to wounds or damaged skin.

When using this product

- Avoid contact with eyes. If product gets into eyes, rinse thoroughly with water
- Do not bandage tightly

Stop use and ask a doctor if:

- Rash appears
- If symptoms persist for more than seven days, discontinue use and consult physician

If pregnant or breastfeeding,

ask a healthcare professional before use.

Keep out of reach of children.

If swallowed get medical help or contact Poison Control Center right away.

Directions

- Apply to affected area 3-4 times daily. Adults and children two-years of age or older:
- Consult a physician Children under two-years of age:

Other Information

- Store at room temperature with lid closed tightly.

Other Ingredients

Aloe Barbadensis (Aloe Vera Gel) Juice, Aqua (Deionized Water), Arnica Montana Extract, AScorbic Acid (Vitamin C), Bosewellia Serrata Extract, Bromelain, Butylene Glycol, C13-14 Isoparaffin, Chamomilla Recutta (Chamomile) Extract, Citric Acid, Curcuma Longa (Turmeric) Extract, Emu Oil, Ethylhexylglycerin, Ethylhexyl Stearate, Glycyrrhiza Glabra (licorice) Root Extract, Helianthus Annuus (Sunflower) Oil, Laureth-7, magnesium Sulfate, Methylsulfonylmethane (MSM), Niacin, Phenoxyethanol, Polyacrylamide, Polysorbate-80, Potassium Sorbate, Sodium Polyacrylate, Tetrasodium EDTA, Tocopheryl Acetate (Vitamin E), Tricedeth-6, Zingiber Officinale (Ginger) Root Extract

Questions or Comments?

(support email address) or Call 1.855.977.0726